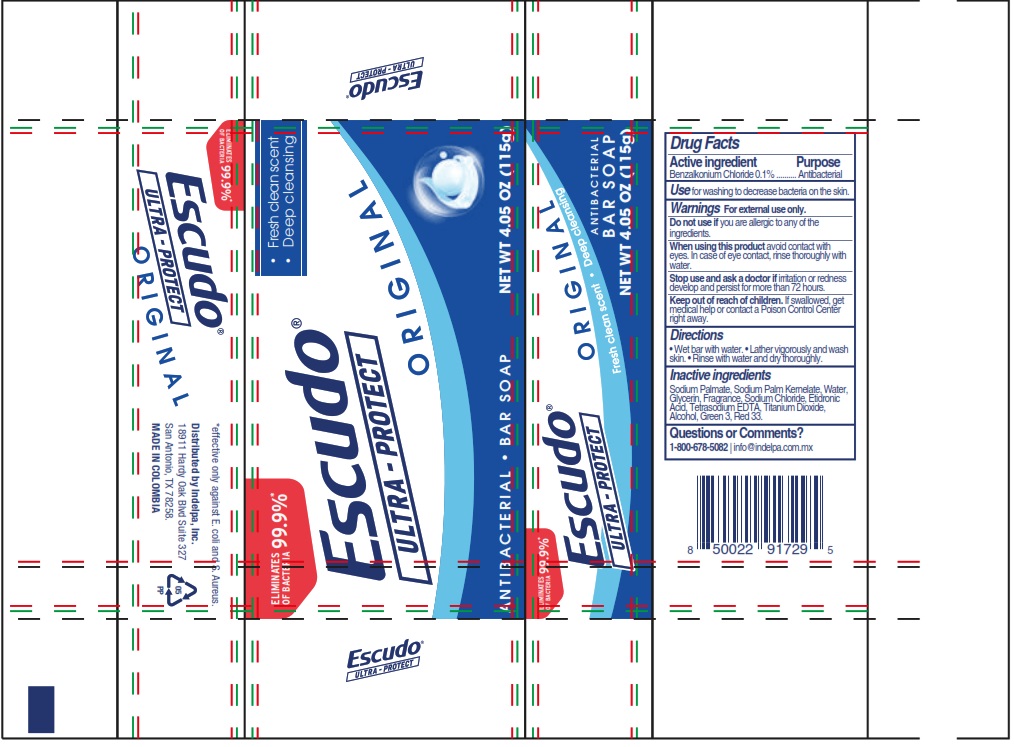 DRUG LABEL: Escudo Ultra-Protect Original
NDC: 84529-001 | Form: SOAP
Manufacturer: Indelpa, Inc
Category: otc | Type: HUMAN OTC DRUG LABEL
Date: 20260203

ACTIVE INGREDIENTS: BENZALKONIUM CHLORIDE 0.1 g/100 g
INACTIVE INGREDIENTS: WATER; ETIDRONIC ACID; GLYCERIN; FD&C GREEN NO. 3; EDETATE SODIUM; D&C RED NO. 33; FRAGRANCE 13576; SODIUM PALMATE; SODIUM CHLORIDE; TITANIUM DIOXIDE; ALCOHOL; SODIUM PALM KERNELATE

Escudo Ultra-Protect Original

Drug Facts

Active Ingredient

Active Ingredient ------------------------------- Purpose

Benzalkonium Chloride 0.1% ----------------- Antibacterial

Active Ingredient ------------------------------- Purpose

Benzalkonium Chloride 0.1% ----------------- Antibacterial

Use

for washing to decrease becateria on the skin.

Warnings

For external use only.

Do not use if

you are allergic to any of the ingredients

Directions

- Wet bar with water.
- Lather vigorously and wash skin.
- Rinse with water and dry thoroughly.

When using this product

avoid contact with eyes. In case of eye contact, rinse thoroughly with water.

Stop use and ask a doctor if

irritation or redness develop and persist for more than 72 hours.

Keep out of reach of children

If swallowed, get medical help or contact a Poison Control Center right away.

Inactive Ingredients

Alcohol, D&C Red 33, Etidronic Acid, FD&C Green 3, Glycerin, Sodium Chloride, Sodium Palmate, Sodium Palm Kernelate, Tetrasodium EDTA, Titanium Dioxide, Water, Fragance.

Questions or Comments?

1-800-678-5082 info@indelpa.com.mx

*effective only against E. coli and S. Aureus.

Distributed by Indelpa, Inc.

18911 Hardy Oak Blvd Suite 327

San Antonio, TX 78258.

MADE IN COLOMBIA

Package Label principal display panel

Eliminates 99.9%

of Bacteria

Fresh clean scent
Deep cleansing

Escudo®

ULTRA-PROTECT

ORIGINAL

ANTIBACTERIAL BAR SOAP

NET WT 4.05 Z (115g)